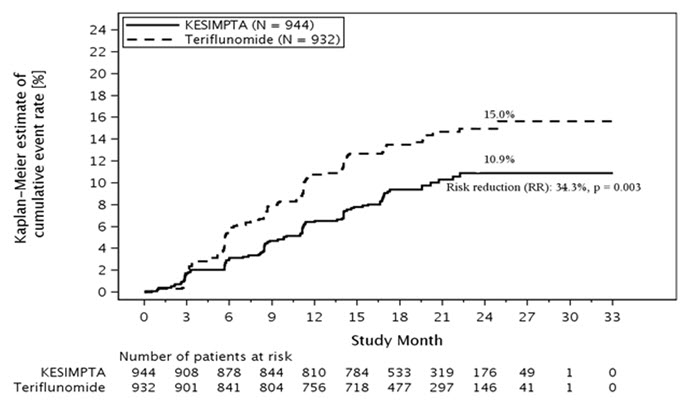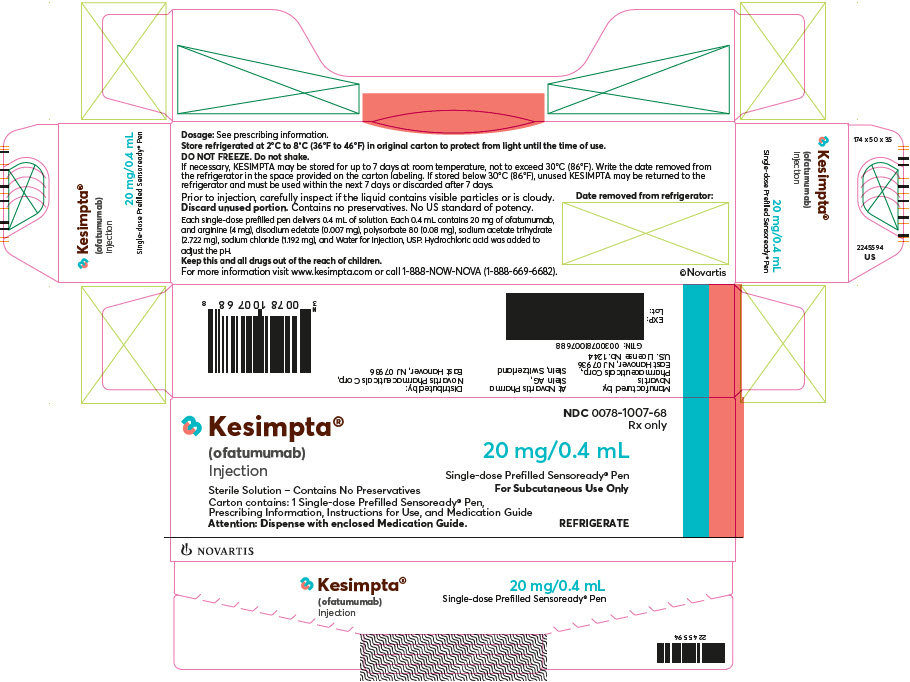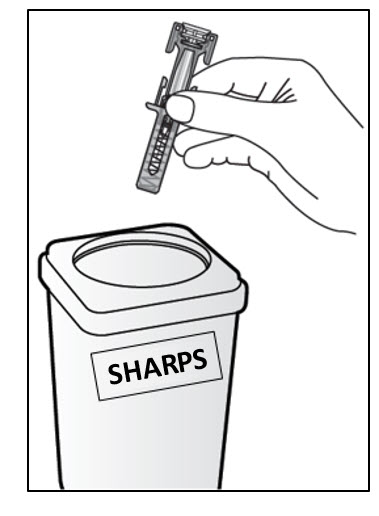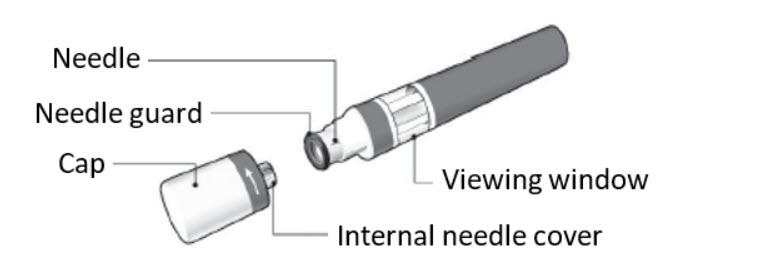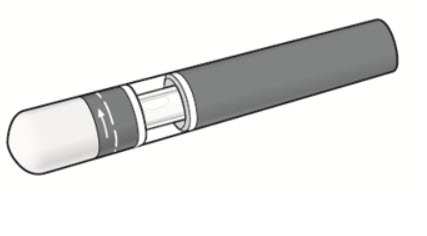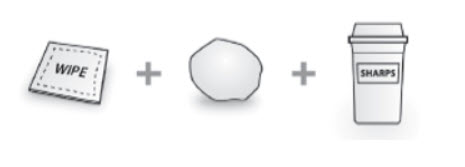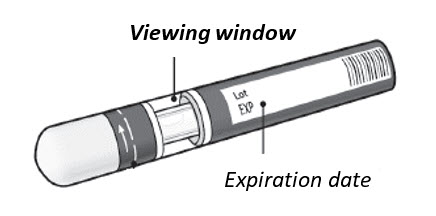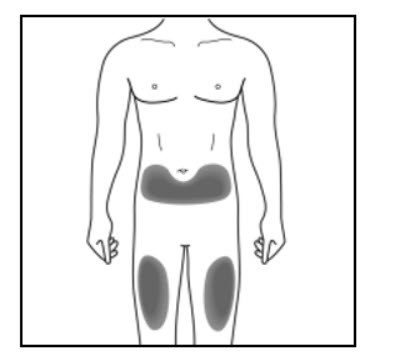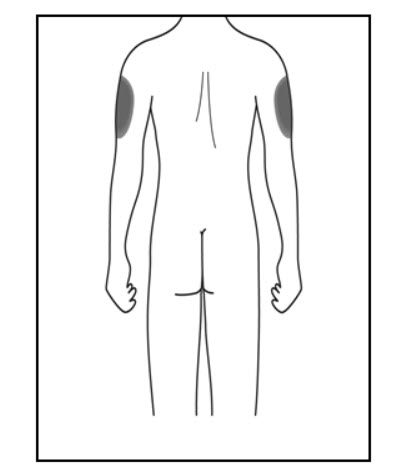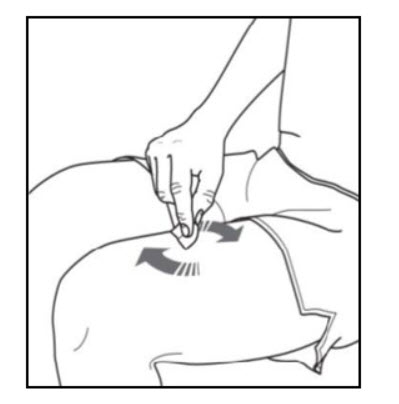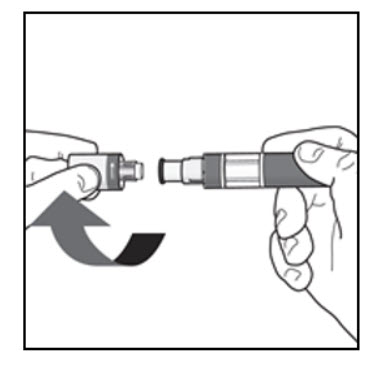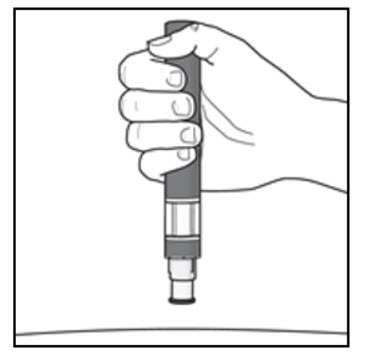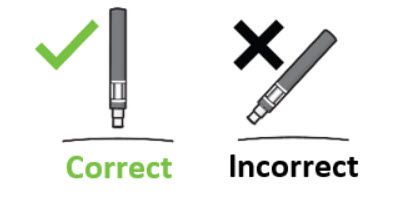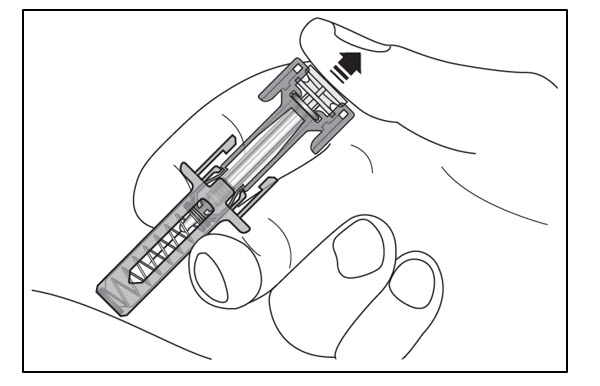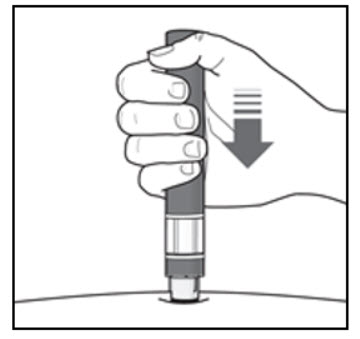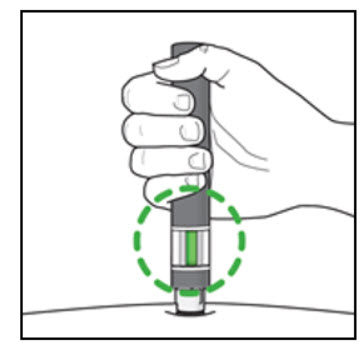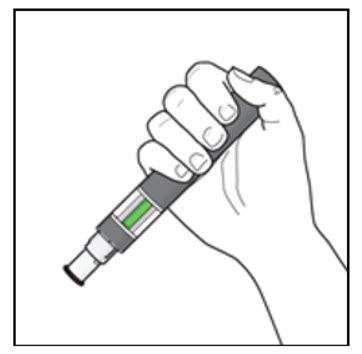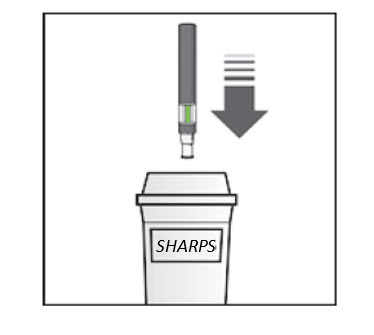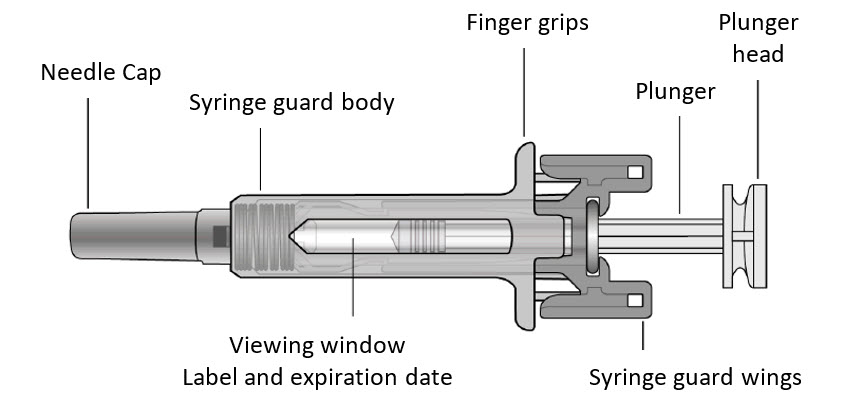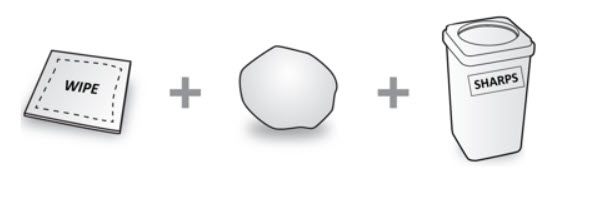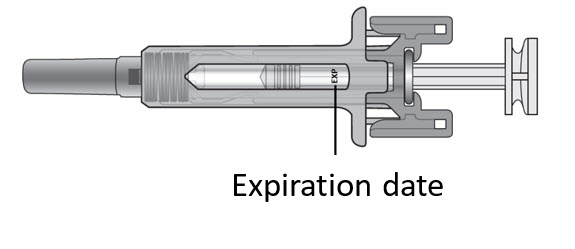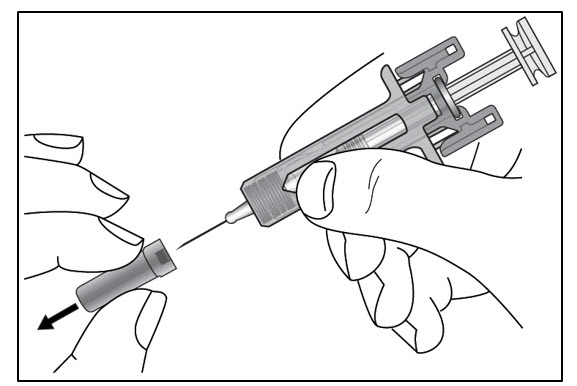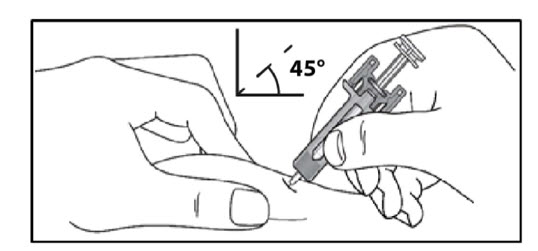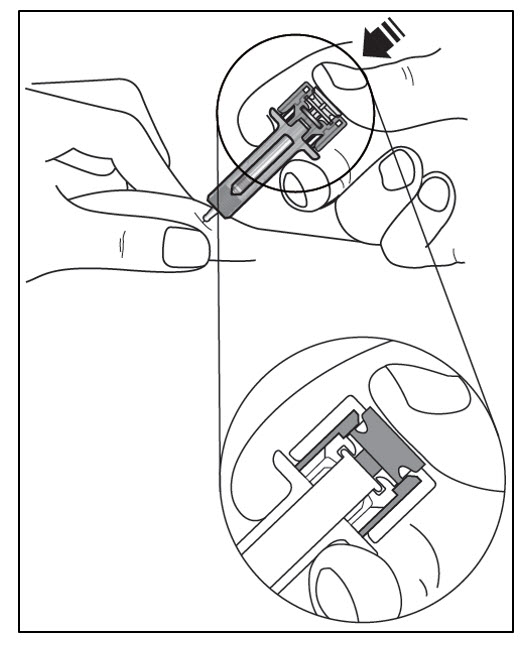 DRUG LABEL: KESIMPTA
NDC: 0078-1007 | Form: INJECTION, SOLUTION
Manufacturer: Novartis Pharmaceuticals Corporation
Category: prescription | Type: HUMAN PRESCRIPTION DRUG LABEL
Date: 20250818

ACTIVE INGREDIENTS: OFATUMUMAB 20 mg/0.4 mL
INACTIVE INGREDIENTS: ARGININE 4.000 mg/0.4 mL; HYDROCHLORIC ACID 5.5 mg/0.4 mL; EDETATE DISODIUM 0.007 mg/0.4 mL; POLYSORBATE 80 0.080 mg/0.4 mL; SODIUM ACETATE 2.722 mg/0.4 mL; SODIUM CHLORIDE 1.192 mg/0.4 mL; WATER

HIGHLIGHTS OF PRESCRIBING INFORMATION

These highlights do not include all the information needed to use KESIMPTA safely and effectively. See full prescribing information for KESIMPTA.
KESIMPTA® (ofatumumab) injection, for subcutaneous use
Initial U.S. Approval: 2009

RECENT MAJOR CHANGES

Dosage and Administration (2.1) | 8/2025
Warnings and Precautions (5.4) | 8/2025

1 INDICATIONS AND USAGE

KESIMPTA is a CD20-directed cytolytic antibody indicated for the treatment of relapsing forms of multiple sclerosis (MS), to include clinically isolated syndrome, relapsing-remitting disease, and active secondary progressive disease, in adults. (1)

2 DOSAGE AND ADMINISTRATION

- Before initiating KESIMPTA, screen for Hepatitis B virus (HBV) and obtain serum quantitative immunoglobulins, aminotransferases, alkaline phosphatase, and bilirubin. (2.1)
- Administer KESIMPTA by subcutaneous injection only. (2.2, 2.3)
- Initial Dosing: 20 mg administered at Weeks 0, 1, and 2. (2.2)
- Subsequent Dosing: 20 mg administered monthly starting at Week 4. (2.2)

3 DOSAGE FORMS AND STRENGTHS

- Injection: 20 mg/0.4 mL solution in a single-dose prefilled Sensoready® Pen (3)
- Injection: 20 mg/0.4 mL solution in a single-dose prefilled syringe (3)

4 CONTRAINDICATIONS

- Active HBV infection. (4)
- History of hypersensitivity to ofatumumab or life-threatening injection-related reaction to KESIMPTA. (4)

5 WARNINGS AND PRECAUTIONS

- Infections: Serious, including life-threatening and fatal infections, have occurred in patients treated with anti-CD20 therapies. Delay KESIMPTA administration in patients with an active infection until the infection is resolved. Vaccination with live-attenuated or live vaccines is not recommended during treatment with KESIMPTA and after discontinuation, until B-cell repletion. (5.1)
- Injection-Related Reactions and Hypersensitivity Reactions: Management for injection-related reactions and hypersensitivity reactions depends on the type and severity of the reaction. (4, 5.2)
- Reduction in Immunoglobulins: Monitor the level of immunoglobulins at the beginning, during, and after discontinuation of treatment with KESIMPTA until B-cell repletion. Consider discontinuing KESIMPTA if a patient develops a serious opportunistic infection or recurrent infections if immunoglobulin levels indicate immune compromise. (5.3)
- Liver Injury: Clinically significant liver injury has occurred. Obtain serum aminotransferases, alkaline phosphatase, and bilirubin levels before initiating KESIMPTA, and during treatment as clinically indicated. Discontinue KESIMPTA in patients with evidence of liver injury in the absence of an alternative etiology. (5.4)
- Fetal Risk: May cause fetal harm based on animal data. Advise females of reproductive potential of the potential risk to a fetus and to use an effective method of contraception during treatment and for 6 months after stopping KESIMPTA. (5.5, 8.1)

6 ADVERSE REACTIONS

Most common adverse reactions (incidence greater than 10%) are upper respiratory tract infection, headache, injection-related reactions, and local injection site reactions. (6.1)
To report SUSPECTED ADVERSE REACTIONS, contact Novartis Pharmaceuticals Corporation at 1-888-669-6682 or FDA at 1-800-FDA-1088 or www.fda.gov/medwatch.

FULL PRESCRIBING INFORMATION

1 INDICATIONS AND USAGE

KESIMPTA is indicated for the treatment of relapsing forms of multiple sclerosis (MS), to include clinically isolated syndrome, relapsing-remitting disease, and active secondary progressive disease, in adults.

2 DOSAGE AND ADMINISTRATION

2.1 Assessments Prior to First Dose of KESIMPTA

Hepatitis B Virus Screening

Prior to initiating KESIMPTA, perform Hepatitis B virus (HBV) screening. KESIMPTA is contraindicated in patients with active HBV confirmed by positive results for Hepatitis B surface antigen [HBsAg] and anti-HBV tests. For patients who are negative for HBsAg and positive for Hepatitis B core antibody [HBcAb+] or are carriers of HBV [HBsAg+], consult liver disease experts before starting and during treatment with KESIMPTA [see Warnings and Precautions (5.1)].

Serum Immunoglobulins

Prior to initiating KESIMPTA, perform testing for quantitative serum immunoglobulins [see Warnings and Precautions (5.3)]. For patients with low serum immunoglobulins, consult immunology experts before initiating treatment with KESIMPTA.

Vaccinations

Because vaccination with live-attenuated or live vaccines is not recommended during treatment and after discontinuation until B-cell repletion, administer all immunizations according to immunization guidelines at least 4 weeks prior to initiation of KESIMPTA for live or live-attenuated vaccines, and whenever possible, at least 2 weeks prior to initiation of KESIMPTA for inactivated vaccines [see Warnings and Precautions (5.1)].

Liver Function Tests

Prior to initiating KESIMPTA, obtain serum aminotransferases (alanine aminotransferase [ALT] and aspartate aminotransferase [AST]), alkaline phosphatase, and bilirubin levels [see Warnings and Precautions (5.4)].

2.2 Recommended Dosage

The recommended dosage of KESIMPTA is:

- initial dosing of 20 mg by subcutaneous injection at Weeks 0, 1, and 2, followed by
- subsequent dosing of 20 mg by subcutaneous injection once monthly starting at Week 4.

Missed Doses

If an injection of KESIMPTA is missed, it should be administered as soon as possible without waiting until the next scheduled dose. Subsequent doses should be administered at the recommended intervals.

2.3 Administration Instructions

Administer by subcutaneous injection only.

KESIMPTA is intended for patient self-administration by subcutaneous injection.

Administer KESIMPTA in the abdomen, thigh, or outer upper arm subcutaneously. Do not give injection into moles, scars, stretch marks, or areas where the skin is tender, bruised, red, scaly, or hard.

The first injection of KESIMPTA should be performed under the guidance of a healthcare professional [see Warnings and Precautions (5.2)].

KESIMPTA Sensoready® pens and syringes are for one-time use only and should be discarded after use. See Instructions for Use for complete administration instructions.

2.4 Preparation of KESIMPTA

The KESIMPTA “Instructions for Use” for each presentation contains more detailed instructions on the preparation of KESIMPTA.

Before administration, remove KESIMPTA Sensoready Pen or KESIMPTA prefilled syringe from the refrigerator and allow KESIMPTA to reach room temperature for about 15 to 30 minutes. DO NOT remove the needle cover while allowing the prefilled syringe to reach room temperature.

Parenteral drug products should be inspected visually for particulate matter and discoloration prior to administration, whenever solution and container permit. Do not use if the liquid contains visible particles or is cloudy.

3 DOSAGE FORMS AND STRENGTHS

KESIMPTA is a clear to slightly opalescent, and colorless to slightly brownish-yellow solution available as follows:

- Injection: 20 mg/0.4 mL in a single-dose prefilled Sensoready Pen
- Injection: 20 mg/0.4 mL in a single-dose prefilled syringe

4 CONTRAINDICATIONS

KESIMPTA is contraindicated in patients with:

- Active HBV infection [see Warnings and Precautions (5.1)].
- History of hypersensitivity to ofatumumab or life-threatening injection-related reaction to KESIMPTA. Hypersensitivity reactions have included anaphylaxis and angioedema [see Warnings and Precautions (5.2)].

5 WARNINGS AND PRECAUTIONS

5.1 Infections

Serious, including life-threatening or fatal, bacterial, fungal, and new or reactivated viral infections have been observed during and following completion of treatment with anti-CD20 B-cell depleting therapies.

In KESIMPTA Study 1 and Study 2 [see Clinical Studies (14)], the overall rate of infections and serious infections in patients treated with KESIMPTA was similar to patients who were treated with teriflunomide (51.6% vs 52.7%, and 2.5% vs 1.8%, respectively). The most common infections reported by KESIMPTA-treated patients in the randomized clinical relapsing MS (RMS) trials included upper respiratory tract infection (39%) and urinary tract infection (10%). Delay KESIMPTA administration in patients with an active infection until the infection is resolved.

Possible Increased Risk of Immunosuppressant Effects with Other Immunosuppressants

When initiating KESIMPTA after an immunosuppressive therapy or initiating an immunosuppressive therapy after KESIMPTA, consider the potential for increased immunosuppressive effects [see Drug Interactions (7.1) and Clinical Pharmacology (12.2)]. KESIMPTA has not been studied in combination with other MS therapies.

Hepatitis B Virus

Reactivation

There were no reports of HBV reactivation in patients with MS treated with KESIMPTA. However, HBV reactivation, in some cases resulting in fulminant hepatitis, hepatic failure, and death, has occurred in patients being treated with ofatumumab for chronic lymphocytic leukemia (CLL) (at higher intravenous doses than the recommended dose in MS but for a shorter duration of treatment) and in patients treated with other anti-CD20 antibodies.

Infection

KESIMPTA is contraindicated in patients with active hepatitis B disease. Fatal infections caused by HBV in patients who have not been previously infected have occurred in patients being treated with ofatumumab for CLL (at higher intravenous doses than the recommended dose in MS but for a shorter duration of treatment). HBV screening should be performed in all patients before initiation of treatment with KESIMPTA. At a minimum, screening should include Hepatitis B surface antigen (HBsAg) and Hepatitis B Core Antibody (HBcAb) testing. These can be complemented with other appropriate markers as per local guidelines. For patients who are negative for HBsAg and positive for HB core antibody [HBcAb+] or are carriers of HBV [HBsAg+], consult liver disease experts before starting and during treatment with KESIMPTA. These patients should be monitored and managed following local medical standards to prevent HBV infection or reactivation.

Progressive Multifocal Leukoencephalopathy

Progressive multifocal leukoencephalopathy (PML) is an opportunistic viral infection of the brain caused by the JC virus (JCV) that typically occurs in patients who are immunocompromised, and that usually leads to death or severe disability.

Although no cases of PML have been reported for KESIMPTA in the RMS clinical studies, PML resulting in death has occurred in patients being treated with ofatumumab for CLL (at substantially higher intravenous doses than the recommended dose in MS but for a shorter duration of treatment). In addition, JCV infection resulting in PML has also been observed in patients treated with other anti-CD20 antibodies and other MS therapies. At the first sign or symptom suggestive of PML, withhold KESIMPTA and perform an appropriate diagnostic evaluation. Magnetic resonance imaging (MRI) findings may be apparent before clinical signs or symptoms. Typical symptoms associated with PML are diverse, progress over days to weeks, and include progressive weakness on one side of the body or clumsiness of limbs, disturbance of vision, and changes in thinking, memory, and orientation leading to confusion and personality changes.

If PML is confirmed, treatment with KESIMPTA should be discontinued.

Vaccinations

Administer all immunizations according to immunization guidelines at least 4 weeks prior to initiation of KESIMPTA for live or live-attenuated vaccines, and whenever possible, at least 2 weeks prior to initiation of KESIMPTA for inactivated vaccines.

KESIMPTA may interfere with the effectiveness of inactivated vaccines.

The safety of immunization with live or live-attenuated vaccines following KESIMPTA therapy has not been studied. Vaccination with live or live-attenuated vaccines is not recommended during treatment and after discontinuation until B-cell repletion [see Clinical Pharmacology (12.2)].

Vaccination of Infants Born to Mothers Treated with KESIMPTA During Pregnancy

In infants of mothers treated with KESIMPTA during pregnancy, do not administer live or live-attenuated vaccines before confirming the recovery of B-cell counts. Depletion of B-cells in these infants may increase the risks from live or live-attenuated vaccines.

Inactivated vaccines may be administered, as indicated, prior to recovery from B-cell depletion, but an assessment of vaccine immune responses, including consultation with a qualified specialist, should be considered to determine whether a protective immune response was mounted.

5.2 Injection-Related Reactions and Hypersensitivity Reactions

KESIMPTA can result in systemic injection-related reactions and hypersensitivity reactions, which may be serious or life-threatening.

In Study 1 and Study 2, systemic and local injection reactions were reported in 21% and 11% of patients treated with KESIMPTA, compared to 15% and 6% of patients treated with teriflunomide who received matching placebo injections, respectively [see Adverse Reactions (6.1) and Clinical Studies (14)].

Injection-related reactions with systemic symptoms observed in clinical studies occurred most commonly within 24 hours of the first injection, but were also observed with later injections. Symptoms observed included fever, headache, myalgia, chills, and fatigue, and were predominantly (99.8%) mild to moderate in severity. There were no life-threatening injection reactions in the RMS clinical studies.

In the post-marketing setting, additional systemic injection-related reactions and hypersensitivity reactions have been reported, including anaphylaxis, angioedema, pruritus, rash, urticaria, erythema, bronchospasm, throat irritation, oropharyngeal pain, dyspnea, pharyngeal or laryngeal edema, flushing, hypotension, dizziness, nausea, and tachycardia. Most cases were non-serious and occurred with the first injection. Most serious cases resulted in permanent discontinuation of KESIMPTA.

Symptoms of systemic injection-related reactions may be clinically indistinguishable from acute hypersensitivity reactions. A hypersensitivity reaction may occur with any injection. New or more severe symptoms compared to those experienced with previous injections should prompt consideration of a potential hypersensitivity reaction.

Only limited benefit of premedication with corticosteroids, antihistamines, or acetaminophen was observed in RMS clinical studies. The first injection of KESIMPTA should be performed under the guidance of an appropriately trained healthcare professional. If systemic injection-related reactions occur, initiate appropriate therapy. Patients who experience symptoms of systemic injection-related reactions or hypersensitivity reactions with KESIMPTA should be instructed to seek immediate medical attention.

If a hypersensitivity reaction or life-threatening systemic injection-related reaction occurs, immediately and permanently discontinue KESIMPTA [see Contraindications (4)]. If restarting KESIMPTA after a severe (but not life-threatening) systemic injection-related reaction or other event after which rechallenge is considered appropriate, administer the next KESIMPTA injection under clinical observation. If a mild to moderate injection-related reaction occurs, consider rechallenge under clinical observation.

Local injection-site reaction symptoms observed in clinical studies included erythema, swelling, itching, and pain. If local injection-related reactions occur, symptomatic treatment is recommended.

5.3 Reduction in Immunoglobulins

As expected with any B-cell depleting therapy, decreased immunoglobulin levels were observed. Decrease in immunoglobulin M (IgM) was reported in 7.7% of patients treated with KESIMPTA compared to 3.1% of patients treated with teriflunomide in RMS clinical trials [see Adverse Reactions (6.1)]. Treatment was discontinued because of decreased immunoglobulins in 3.4% of patients treated with KESIMPTA and in 0.8% of patients treated with teriflunomide. No decline in immunoglobulin G (IgG) was observed at the end of the study. Monitor the levels of quantitative serum immunoglobulins during treatment, especially in patients with opportunistic or recurrent infections, and after discontinuation of therapy until B-cell repletion. Consider discontinuing KESIMPTA therapy if a patient with low immunoglobulins develops a serious opportunistic infection or recurrent infections, or if prolonged hypogammaglobulinemia requires treatment with intravenous immunoglobulins.

5.4 Liver Injury

Clinically significant liver injury, without findings of viral hepatitis, has been reported in the postmarketing setting in patients treated with anti-CD20 B-cell depleting therapies approved for the treatment of MS, including KESIMPTA. Signs of liver injury, including markedly elevated serum hepatic enzymes with elevated total bilirubin, have occurred weeks to months after administration.

Patients treated with KESIMPTA found to have an alanine aminotransferase (ALT) or aspartate aminotransferase (AST) greater than 3x the upper limit of normal (ULN) with serum total bilirubin greater than 2x ULN, are potentially at risk for severe drug-induced liver injury.

Obtain liver function tests prior to initiating treatment with KESIMPTA [see Dosage and Administration (2.1)], and monitor for signs and symptoms of any hepatic injury during treatment. Measure serum aminotransferases, alkaline phosphatase, and bilirubin levels promptly in patients who report symptoms that may indicate liver injury, including new or worsening fatigue, anorexia, nausea, vomiting, right upper abdominal discomfort, dark urine, or jaundice. If liver injury is present and an alternative etiology is not identified, discontinue KESIMPTA.

5.5 Fetal Risk

Based on animal data, KESIMPTA can cause fetal harm due to B-cell lymphopenia and reduce antibody response in offspring exposed to KESIMPTA in utero. Transient peripheral B-cell depletion and lymphocytopenia have been reported in infants born to mothers exposed to other anti-CD20 B-cell depleting antibodies during pregnancy. Advise females of reproductive potential to use effective contraception while receiving KESIMPTA and for at least 6 months after the last dose [see Use in Specific Populations (8.1)].

6 ADVERSE REACTIONS

The following clinically significant adverse reactions are discussed in greater detail elsewhere in the labeling:

- Infections [see Warnings and Precautions (5.1)]
- Injection-Related Reactions and Hypersensitivity Reactions [see Warnings and Precautions (5.2)]
- Reduction in Immunoglobulins [see Warnings and Precautions (5.3)]
- Liver Injury [see Warnings and Precautions (5.4)]

6.1 Clinical Trials Experience

Because clinical trials are conducted under widely varying conditions, adverse reaction rates observed in the clinical trials of a drug cannot be directly compared to rates in the clinical trials of another drug and may not reflect the rates observed in clinical practice.

Approximately 1500 patients with RMS received KESIMPTA in clinical studies. In Study 1 and Study 2, 1882 patients with RMS were randomized, 946 of whom were treated with KESIMPTA for a median duration of 85 weeks; 33% of patients receiving KESIMPTA were treated for up to 120 weeks [see Clinical Studies (14.1)]. The most common adverse reactions occurring in greater than 10% of patients treated with KESIMPTA and more frequently than in patients treated with teriflunomide were upper respiratory tract infections, injection-related reactions (systemic), headache, and injection-site reactions (local). The most common cause of discontinuation in patients treated with KESIMPTA was low immunoglobulin M (3.3%), defined in trial protocols as IgM at 10% below the lower limit of normal (LLN).

Table 1 summarizes the adverse drug reactions that occurred in Study 1 and Study 2.

Table 1: Adverse Reactions in Patients With RMS With an Incidence of at Least 5% With KESIMPTA and a Greater Incidence Than Teriflunomide (Pooled Study 1 and Study 2)
Adverse reactions | KESIMPTA 20 mg N = 946 % | Teriflunomide 14 mg N = 936 %
Upper respiratory tract infectionsa | 39 | 38
Injection-related reactions (systemic) | 21 | 15
Headache | 13 | 12
Injection-site reactions (local) | 11 | 6
Urinary tract infection | 10 | 8
Back pain | 8 | 6
Blood immunoglobulin M decreased | 6 | 2
aIncludes the following: nasopharyngitis, upper respiratory tract infection, influenza, sinusitis, pharyngitis, rhinitis, viral upper respiratory infection, tonsillitis, acute sinusitis, pharyngotonsillitis, laryngitis, pharyngitis streptococcal, viral rhinitis, sinusitis bacterial, tonsillitis bacterial, viral pharyngitis, viral tonsillitis, chronic sinusitis, nasal herpes, tracheitis.

Injection-Related Reactions and Injection-Site Reactions

The incidence of injection-related reactions (systemic) was highest with the first injection (14.4%), decreasing with subsequent injections (4.4% with second, less than 3% with third injection). Injection-related reactions were mostly (99.8%) mild to moderate in severity. Two (0.2%) patients treated with KESIMPTA reported serious injection-related reactions. There were no life-threatening injection-related reactions. Most frequently reported symptoms (2% or greater) included fever, headache, myalgia, chills, and fatigue.

In addition to systemic injection-related reactions, local reactions at the administration site were very common. Local injection-site reactions were all mild to moderate in severity. The most frequently reported symptoms (2% or greater) included erythema, pain, itching, and swelling [see Warnings and Precautions (5.2)].

Laboratory Abnormalities

Immunoglobulins

In Study 1 and Study 2, a decrease in the mean level of IgM was observed in KESIMPTA-treated patients but was not associated with an increased risk of infections [see Warnings and Precautions (5.3)]. In 14.3% of patients in Study 1 and Study 2, treatment with KESIMPTA resulted in a decrease in a serum IgM that reached a value below 0.34 g/L. KESIMPTA was associated with a decrease of 4.3% in mean IgG levels after 48 weeks of treatment and an increase of 2.2% after 96 weeks.

6.2 Immunogenicity

As with all therapeutic proteins, there is potential for immunogenicity. The detection of antibody formation is highly dependent on the sensitivity and specificity of the assay. Additionally, the observed incidence of antibody (including neutralizing antibody) positivity in an assay may be influenced by several factors, including assay methodology, sample handling, timing of sample collection, concomitant medication, and the underlying disease. For these reasons, comparison of the incidence of antibodies in the studies described below with the incidence of antibodies in other studies or to other ofatumumab products may be misleading.

Treatment-induced anti-drug antibodies (ADAs) were detected in 2 of 914 (0.2%) KESIMPTA-treated patients; no patients with treatment-enhancing or neutralizing ADAs were identified. There was no impact of positive ADA titers on pharmacokinetics, safety profile or B-cell kinetics in any patient; however, these data are not adequate to assess the impact of ADAs on the safety and efficacy of KESIMPTA.

6.3 Postmarketing Experience

The following adverse reactions have been identified during postapproval use of KESIMPTA. Because these reactions are reported voluntarily from a population of uncertain size, it is not always possible to reliably estimate their frequency or establish a causal relationship to drug exposure.

Immune System: Hypersensitivity reactions [see Warnings and Precautions (5.2)]

Hepatobiliary Disorders: Liver injury [see Warnings and Precautions (5.4)]

7 DRUG INTERACTIONS

7.1 Immunosuppressive or Immune-Modulating Therapies

Concomitant usage of KESIMPTA with immunosuppressant drugs, including systemic corticosteroids, may increase the risk of infection. Consider the risk of additive immune system effects when coadministering immunosuppressive therapies with KESIMPTA.

When switching from therapies with immune effects, the duration and mechanism of action of these therapies should be taken into account because of potential additive immunosuppressive effects when initiating KESIMPTA.

8 USE IN SPECIFIC POPULATIONS

8.1 Pregnancy

Pregnancy Exposure Registry

There is a pregnancy exposure registry that monitors pregnancy outcomes in women exposed to KESIMPTA during pregnancy. Healthcare providers are encouraged to enroll pregnant patients, or pregnant women may register themselves in the MotherToBaby Pregnancy Study in Multiple Sclerosis by calling 1-877-311-8972, by sending an email to MotherToBaby@health.ucsd.edu, or by going to www.mothertobaby.org/join-study.

Risk Summary

There are no adequate data on the developmental risk associated with the use of KESIMPTA in pregnant women. Ofatumumab may cross the placenta and cause fetal B-cell depletion based on findings from animal studies (see Data).

Transient peripheral B-cell depletion and lymphocytopenia have been reported in infants born to mothers exposed to other anti-CD20 antibodies during pregnancy. B-cell levels in infants following maternal exposure to KESIMPTA have not been studied in clinical trials. The potential duration of B-cell depletion in infants exposed to ofatumumab in utero, and the impact of B-cell depletion on the safety and effectiveness of vaccines, are unknown. Avoid administering live vaccines to neonates and infants exposed to KESIMPTA in utero until B-cell recovery occurs [see Warnings and Precautions (5.2) and Clinical Pharmacology (12.2)].

Following administration of ofatumumab to pregnant monkeys, increased mortality, depletion of B-cell populations, and impaired immune function were observed in the offspring, in the absence of maternal toxicity, at plasma levels substantially higher than that in humans (see Data).

In the U.S. general population, the estimated background risk of major birth defects and miscarriage in clinically recognized pregnancies is 2% to 4% and 15% to 20%, respectively. The background risk of major birth defects and miscarriage for the indicated population is unknown.

Data

Animal Data

Intravenous administration of ofatumumab (weekly doses of 0, 20, or 100 mg/kg) to pregnant monkeys during the period of organogenesis (gestations days 20 to 50) resulted in no adverse effects on embryofetal development; however, B-cell depletion was observed in fetuses at both doses when assessed on gestation day 100. Plasma exposure (Cave) at the no-effect dose (100 mg/kg) for adverse effects on embryofetal development was greater than 5000 times that in humans at the recommended human maintenance dose of 20 mg. A no-effect dose for effects on B-cells was not identified; plasma exposure (Cave) at the low-effect dose (20 mg/kg) was approximately 780 times that in humans at the recommended human maintenance dose (RHMD) of 20 mg/month.

Intravenous administration of ofatumumab (5 weekly doses of 0, 10, and 100 mg/kg, followed by biweekly doses of 0, 3, and 20 mg/kg) to pregnant monkeys throughout pregnancy resulted in no adverse effects on the development of the offspring. However, postnatal death, B-cell depletion, and impaired immune function were observed in the offspring at the high dose. The deaths at the high dose were considered secondary to B-cell depletion. Plasma exposure (Cave) in dams at the no-effect dose (100/20 mg/kg) for adverse developmental effects was approximately 500 times that in humans at RHMD. A no-effect level for mortality and immune effects in offspring was not established because of the limited number of evaluable offspring at the low dose.

8.2 Lactation

Risk Summary

There are no data on the presence of ofatumumab in human milk, the effects on the breastfed infant, or the effects of the drug on milk production. Human IgG is excreted in human milk, and the potential for absorption of ofatumumab to lead to B-cell depletion in the infant is unknown. The developmental and health benefits of breastfeeding should be considered along with the mother’s clinical need for KESIMPTA and any potential adverse effects on the breastfed infant from KESIMPTA or from the underlying maternal condition.

8.3 Females and Males of Reproductive Potential

Contraception

Females of childbearing potential should use effective contraception while receiving KESIMPTA and for 6 months after the last treatment of KESIMPTA [see Warnings and Precautions (5.5) and Clinical Pharmacology (12.3)].

8.4 Pediatric Use

Safety and effectiveness in pediatric patients have not been established.

8.5 Geriatric Use

Clinical studies of KESIMPTA did not include sufficient numbers of geriatric patients to determine whether they respond differently from younger subjects.

11 DESCRIPTION

Ofatumumab is a recombinant human monoclonal immunoglobulin G1 (IgG1) antibody that binds to human CD20 expressed on B-cells. Ofatumumab is produced in a murine NS0 cell line and consists of two IgG1 heavy chains and two kappa light chains with a molecular weight of approximately 146 kDa.

KESIMPTA (ofatumumab) injection is a sterile, preservative-free solution for subcutaneous use.

Each 20 mg/0.4 mL KESIMPTA Sensoready Pen or prefilled syringe delivers 0.4 mL of solution. Each 0.4 mL contains 20 mg of ofatumumab, and arginine (4 mg), disodium edetate (0.007 mg), polysorbate 80 (0.08 mg), sodium acetate trihydrate (2.722 mg), sodium chloride (1.192 mg), and Water for Injection, USP with a pH of 5.5. Hydrochloric acid may have been added to adjust pH.

12 CLINICAL PHARMACOLOGY

12.1 Mechanism of Action

The precise mechanism by which ofatumumab exerts its therapeutic effects in multiple sclerosis is unknown, but is presumed to involve binding to CD20, a cell surface antigen present on pre-B and mature B lymphocytes. Following cell surface binding to B lymphocytes, ofatumumab results in antibody-dependent cellular cytolysis and complement-mediated lysis.

12.2 Pharmacodynamics

B-cell Depletion

For B-cell counts, assays for CD19+ B-cells are used because the presence of ofatumumab interferes with the CD20 assay. In Study 1 and Study 2, KESIMPTA administered as recommended, resulted in a reduction of CD19+ B-cells to below the LLN in 77.0% and 78.8% of patients, respectively, one week after treatment initiation, and in 95.0% and 95.8% of patients, respectively, two weeks after treatment initiation [see Dosage and Administration (2.2) and Clinical Studies (14)]. In Study 1 and Study 2, at Week 12, 99.3% to 99.5% of patients had CD19+ B-cell counts below LLN. The CD19+ B-cell counts remained below LLN for approximately 97% of patients in Study 1 and 92% of patients in Study 2 from 12 weeks through 120 weeks while on KESIMPTA treatment.

In a study of bioequivalence using the same dosing regimen as in Study 1 and Study 2, before initiation of the maintenance phase, total CD19+ B-cell levels below the defined threshold of 10 cells/µL were achieved in 94% of patients starting at Week 4 and 98% of patients at Week 12.

B-cell Repletion

Data from Studies 1 and 2 indicate a median time to B-cell recovery to either LLN or baseline value of 24.6 weeks post-treatment discontinuation. Pharmacokinetics and pharmacodynamics modeling and simulation for B-cell repletion corroborate these data, predicting median time to B-cell recovery to LLN of 23 weeks post-treatment discontinuation.

12.3 Pharmacokinetics

Absorption

A subcutaneous dose of 20 mg every 4 weeks leads to a mean AUCtau of 483 mcg h/mL and a mean Cmax of 1.43 mcg/mL at steady state.

After subcutaneous administration, ofatumumab is believed to be predominantly absorbed via the lymphatic system similarly to other therapeutic monoclonal antibodies.

Distribution

The volume of distribution at steady-state was estimated to be 5.42 L following subcutaneous administration of repeated KESIMPTA 20 mg dose.

Elimination

Ofatumumab is eliminated by both linear catabolic pathways and a non-linear B-cell mediated pathway, resulting in non-constant elimination half-life. Initially, a higher baseline B-cell count results in greater B-cell-mediated elimination and shorter ofatumumab half-life. As the B-cells are depleted, the catabolic pathway predominates, resulting in a relatively longer ofatumumab half-life compared to earlier in therapy when both elimination pathways were available. Following B-cell depletion, clearance was estimated to be 0.34 L/day following repeated subcutaneous administration of KESIMPTA 20 mg injections. The half-life at steady state was estimated to be approximately 16 days following subcutaneous administration of repeated KESIMPTA 20 mg dosage.

Metabolism

Ofatumumab is a protein for which the expected metabolic pathway is degradation to small peptides and amino acids by ubiquitous proteolytic enzymes.

Excretion

Ofatumumab, a monoclonal antibody, is not likely to undergo renal excretion.

Specific Populations

The following population characteristics do not have a clinically meaningful effect on the pharmacokinetics of ofatumumab: body weight, sex, age, race, or baseline B-cell count.

Patients with Renal/Hepatic Impairment

Pharmacokinetics of ofatumumab in patients with renal or hepatic impairment have not been studied.

Drug Interaction Studies

Ofatumumab does not share a common clearance pathway with chemical drugs that are metabolized by the cytochrome P450 system or other drug-metabolizing enzymes. Additionally, there is no evidence that CD20 monoclonal antibodies are involved in the regulation of the expression of drug-metabolizing enzymes. Interactions between KESIMPTA and other medicinal products have not been investigated in formal studies.

13 NONCLINICAL TOXICOLOGY

13.1 Carcinogenesis, Mutagenesis, Impairment of Fertility

Carcinogenesis

No carcinogenicity studies have been conducted to assess the carcinogenic potential of ofatumumab.

Mutagenesis

No studies have been conducted to assess the mutagenic potential of ofatumumab. As an antibody, ofatumumab is not expected to interact directly with DNA.

Impairment of Fertility

No effects on reproductive parameters, including hormones, menstrual cycle, sperm analysis, or histopathological evaluation of reproductive organs, were observed in male or female monkeys administered ofatumumab by intravenous injection (5 weekly doses of 0, 10, and 100 mg/kg, followed by biweekly doses of 0, 3, and 20 mg/kg). Plasma exposures (Cave) at the high dose tested in monkeys are greater than 500 times that in humans at the recommended human maintenance dose of 20 mg/month.

14 CLINICAL STUDIES

The efficacy of KESIMPTA was demonstrated in two randomized, double-blind, double-dummy, active comparator-controlled clinical trials of identical design, in patients with relapsing forms of MS [Study 1 (NCT02792218) and Study 2 (NCT02792231)]. Both studies enrolled patients with at least one relapse in the previous year, 2 relapses in the previous 2 years, or the presence of a T1 gadolinium-enhancing (GdE) lesion in the previous year. Patients were also required to have an Expanded Disability Status Scale (EDSS) score from 0 to 5.5.

Patients were randomized to receive either KESIMPTA, 20 mg subcutaneously on Days 1, 7, and 14, followed by 20 mg every 4 weeks thereafter starting at Week 4 with a daily oral placebo, or the active comparator, teriflunomide, at a dose of 14 mg orally once daily with a placebo administered subcutaneously on Days 1, 7, 14, and every 4 weeks thereafter. The treatment duration for an individual patient was variable based on when the end-of-study criteria were met. The maximal duration of treatment for an individual patient was 120 weeks. Neurologic evaluations were performed at baseline, every 3 months during blinded treatment, and at the time of a suspected relapse. Brain MRI scans were performed at baseline, 1 year, and 2 years.

The primary endpoint of both trials was the annualized relapse rate (ARR) over the treatment period. Additional outcome measures included: 1) the time to 3-month confirmed disability progression for the pooled populations, 2) the number of T1 GdE lesions per scan at Weeks 48 and 96, and 3) the annualized rate of new or enlarging T2 MRI lesions. Disability progression was defined as an increase in EDSS of at least 1.5, 1, or 0.5 points in patients with a baseline EDSS of 0, 1 to 5, or 5.5 or greater, respectively.

In Study 1, a total of 927 patients were randomized to receive KESIMPTA (n = 465) or teriflunomide (n = 462). Of those randomized to KESIMPTA, 90% completed the study; of those randomized to teriflunomide, 81% completed the study. Demographics and disease characteristics were balanced across treatment arms. The mean age was 38 years, 89% were White, and 69% were female. The mean time since MS diagnosis was 5.7 years and the median EDSS score at baseline was 3.0; 60% had been treated with a non-steroid therapy for MS. At baseline, the mean number of relapses in the previous year was 1 and the mean number of T1 GdE lesions on MRI scan was 1.5.

In Study 2, a total of 955 patients were randomized to receive KESIMPTA (n = 481) or teriflunomide (n = 474). Of those randomized to KESIMPTA, 83% completed the study; of those randomized to teriflunomide, 82% completed the study. Demographics and disease characteristics were balanced across treatment arms. The mean age was 38 years, 87% were White, and 67% were female. The mean time since MS diagnosis was 5.5 years and the median EDSS score at baseline was 2.5; 61% had been treated with a non-steroid therapy for MS. At baseline, the mean number of relapses in the previous year was 1.3, and the mean number of T1 GdE lesions on MRI scan was 1.6.

In both studies, KESIMPTA significantly lowered the ARR compared to teriflunomide.

KESIMPTA significantly reduced the risk of 3-month confirmed disability progression compared to teriflunomide.

KESIMPTA significantly reduced the number of T1 GdE lesions and the rate of new or enlarging T2 lesions in both studies.

Key results for Study 1 and Study 2 are presented in Table 2 and Figure 1.

Table 2: Key Clinical and MRI Endpoints From Study 1 and Study 2
 | Study 1 |  | Study 2
Endpoints | KESIMPTA 20 mg (n = 465) | Teriflunomide 14 mg (n = 462) | KESIMPTA 20 mg (n = 481) | Teriflunomide 14 mg (n = 474)
Clinical Endpoints
Annualized relapse rate (primary endpoint) | 0.11 | 0.22 | 0.10 | 0.25
Relative reduction | 51% (p < 0.001) |  | 58% (p < 0.001)
Proportion of patients with 3-month confirmed disability progressiona,b Relative risk reduction | 10.9% KESIMPTA vs 15.0% teriflunomide 34.3% (p = 0.003)
MRI Endpoints
Mean number of T1 Gd-enhancing lesions per MRI scan | 0.01 | 0.46 | 0.03 | 0.52
Relative reduction | 98% (p < 0.001) |  | 94% (p < 0.001)
Number of new or enlarging T2 lesions per year | 0.72 | 4.00 | 0.64 | 4.16
Relative reduction | 82% (p < 0.001) |  | 85% (p < 0.001)
aDisability progression was defined as an increase in EDSS of at least 1.5, 1, or 0.5 points in patients with a baseline EDSS of 0, 1 to 5, or 5.5 or greater, respectively.
bProspective pooled analysis of Studies 1 and 2. Proportion of patients with 3-month confirmed disability progression refers to Kaplan-Meier estimates at Month 24.

Figure 1: Time to First 3-month Confirmed Disability Progression by Treatment Full Analysis Set

A similar effect of KESIMPTA on the key efficacy results compared to teriflunomide was observed across the two studies in exploratory subgroups defined by sex, age, body weight, prior non-steroid MS therapy, and baseline disability and disease activity.

16 HOW SUPPLIED/STORAGE AND HANDLING

16.1 How Supplied

KESIMPTA (ofatumumab) injection is a preservative-free, clear to slightly opalescent and colorless to slightly brownish-yellow solution for subcutaneous administration, which is supplied as follows:

KESIMPTA Sensoready Pen:

Carton of one 20 mg/0.4 mL single-dose prefilled Sensoready Pen NDC 0078-1007-68

KESIMPTA Prefilled Syringe:

Carton of one 20 mg/0.4 mL single-dose prefilled syringe NDC 0078-1007-69

16.2 Storage and Handling

KESIMPTA Sensoready pens and prefilled syringes must be refrigerated at 2ºC to 8ºC (36ºF to 46ºF). Keep the product in the original carton to protect from light until the time of use. Do not freeze. To avoid foaming, do not shake.

If necessary, KESIMPTA may be stored for up to 7 days at room temperature, not to exceed 30°C (86°F). Write the date removed from the refrigerator in the space provided on the carton labeling. If stored below 30°C (86°F), unused KESIMPTA may be returned to the refrigerator and must be used within the next 7 days or discarded after 7 days.

17 PATIENT COUNSELING INFORMATION

Advise the patient to read FDA-approved patient labeling (Medication Guide and Instructions for Use).

Infections

Advise patients to contact their healthcare provider for any signs of infection during treatment or after the last dose. Signs include fever, chills, constant cough, or dysuria [see Warnings and Precautions (5.1)].

Advise patients that KESIMPTA may cause reactivation of hepatitis B infection and that monitoring will be required if they are at risk [see Warnings and Precautions (5.1)].

Advise patients that PML has happened with an intravenous form of ofatumumab administered at a higher intravenous dosage in patients with CLL, as well as with drugs that are similar to KESIMPTA, and may happen with KESIMPTA. Inform the patient that PML is characterized by a progression of deficits and usually leads to death or severe disability over weeks or months. Instruct the patient of the importance of contacting their healthcare provider if they develop any symptoms suggestive of PML. Inform the patient that typical symptoms associated with PML are diverse, progress over days to weeks, and include progressive weakness on one side of the body or clumsiness of limbs, disturbance of vision, and changes in thinking, memory, and orientation leading to confusion and personality changes [see Warnings and Precautions (5.1)].

Vaccinations

Advise patients to complete any required live or live-attenuated vaccinations at least 4 weeks and, whenever possible at least 2 weeks, prior to initiation of KESIMPTA for inactivated vaccines.

Administration of live-attenuated or live vaccines is not recommended during KESIMPTA treatment and until B-cell recovery [see Warnings and Precautions (5.1)].

Injection-Related Reactions and Hypersensitivity Reactions

Inform patients about the signs and symptoms of injection-related reactions and hypersensitivity reactions. Inform patients that injection-related reactions generally occur within 24 hours and predominantly following the first injection. A hypersensitivity reaction may occur with any injection, and any new or worsening symptoms with subsequent KESIMPTA injections should prompt consideration of a hypersensitivity reaction. Advise patients to seek immediate medical attention if they experience signs or symptoms of a severe or life-threatening injection-related reaction or hypersensitivity reaction, and to contact their healthcare provider if they experience any signs or symptoms of an injection-related reaction or hypersensitivity reaction [see Warnings and Precautions (5.2)].

Liver Injury

Inform patients that liver injury has been reported with anti-CD20 B-cell depleting therapies, including KESIMPTA. Instruct patients treated with KESIMPTA to promptly report any symptoms that may indicate liver injury, including fatigue, anorexia, nausea, vomiting, right upper abdominal discomfort, dark urine, or jaundice. A blood test should be obtained before patients start therapy, and during treatment as clinically indicated [see Warnings and Precautions (5.4)].

Contraception

Advise females of childbearing potential to use effective contraception while receiving KESIMPTA and for 6 months after the last treatment of KESIMPTA [see Warnings and Precautions (5.5) and Use in Specific Populations (8.3)].

Pregnancy Exposure Registry

Instruct patients that if they are pregnant or plan to become pregnant while taking KESIMPTA, they should inform their healthcare provider. Encourage patients to enroll in the MotherToBaby Pregnancy Study in Multiple Sclerosis if they become pregnant while taking KESIMPTA [see Use in Specific Populations (8.1)].

Instruction on Injection Technique

Patients or caregivers should be instructed by a healthcare professional on how to administer KESIMPTA [see Instructions for Use].

Instruct patients or caregivers in the technique of proper syringe and needle disposal, and advise them not to reuse these items. Instruct patients to inject the full amount of KESIMPTA according to the directions provided in the Instructions for Use. Dispose of pens and syringes in a puncture-resistant container.

Manufactured by:
Novartis Pharmaceuticals Corporation
East Hanover, NJ 07936
U.S. License No.: 1244

KESIMPTA and SENSOREADY are [registered] trademarks of Novartis AG.

T2025-49

MEDICATION GUIDE

KESIMPTA® (KEY-simp-ta)
(ofatumumab)
injection, for subcutaneous use

What is the most important information I should know about KESIMPTA?
KESIMPTA can cause serious side effects, including:
Infections. Serious infections, which can be life-threatening or cause death, can happen during treatment with KESIMPTA. If you have an active infection, your healthcare provider should delay your treatment with KESIMPTA until your infection is gone. KESIMPTA taken before or after other medicines that weaken the immune system may increase your risk of getting infections.
Tell your healthcare provider right away if you have any infections or get any symptoms, including painful and frequent urination, nasal congestion, runny nose, sore throat, fever, chills, cough, or body aches.

- Hepatitis B virus (HBV) reactivation. Before starting treatment with KESIMPTA, your healthcare provider will do blood tests to check for HBV. If you have ever had HBV infection, the HBV may become active again during or after treatment with KESIMPTA. Hepatitis B virus becoming active again (called reactivation) may cause serious liver problems, including liver failure or death. You should not receive KESIMPTA if you have active hepatitis B liver disease. Your healthcare provider will monitor you for HBV infection during and after you stop using KESIMPTA.

Tell your healthcare provider right away if you get worsening tiredness or yellowing of your skin or white part of your eyes during treatment with KESIMPTA.

- Progressive Multifocal Leukoencephalopathy (PML). PML may happen with KESIMPTA. PML is a rare, serious brain infection caused by a virus that may get worse over days or weeks. PML can result in death or severe disability. Tell your healthcare provider right away if you have any new or worsening neurologic signs or symptoms. These may include weakness on one side of your body, loss of coordination in arms and legs, vision problems, changes in thinking and memory which may lead to confusion and personality changes.
- Weakened immune system. KESIMPTA taken before or after other medicines that weaken the immune system could increase your risk of getting infections.

What is KESIMPTA?
KESIMPTA is a prescription medicine used to treat adults with relapsing forms of multiple sclerosis (MS), including:

- clinically isolated syndrome
- relapsing-remitting disease
- active secondary progressive disease

It is not known if KESIMPTA is safe or effective in children.

Do not use KESIMPTA if you:

- have an active hepatitis B virus infection.
- have had an allergic reaction to ofatumumab or life-threatening injection-related reaction to KESIMPTA. See the end of this Medication Guide for a complete list of ingredients in KESIMPTA.

Before using KESIMPTA, tell your healthcare provider about all of your medical conditions, including if you:

- have or think you have an infection, including HBV or PML. See “What is the most important information I should know about KESIMPTA?”
- have ever taken, currently take, or plan to take medicines that affect your immune system. These medicines could increase your risk of getting an infection.
- have a history of liver problems.
- have had a recent vaccination or are scheduled to receive any vaccinations.
  - You should receive any required ‘live’ or ‘live-attenuated’ vaccines at least 4 weeks before you start treatment with KESIMPTA. You should not receive ‘live’ or ‘live-attenuated’ vaccines while you are being treated with KESIMPTA and until your healthcare provider tells you that your immune system is no longer weakened.
  - Whenever possible, you should receive any ‘non-live’ vaccines at least 2 weeks before you start treatment with KESIMPTA.
  - Talk to your healthcare provider about vaccinations for your baby if you used KESIMPTA during your pregnancy.
- are pregnant, think that you might be pregnant, or plan to become pregnant. It is not known if KESIMPTA will harm your unborn baby. Females who can become pregnant should use birth control (contraception) during treatment with KESIMPTA and for 6 months after your last treatment. Talk with your healthcare provider about what birth control method is right for you during this time.
  - Pregnancy Registry: There is a registry for women who become pregnant during treatment with KESIMPTA. If you become pregnant while taking KESIMPTA, tell your healthcare provider right away. Talk to your healthcare provider about registering with the MotherToBaby Pregnancy Study in Multiple Sclerosis. The purpose of the registry is to collect information about your health and your baby’s health. For more information or to register, contact MotherToBaby by calling 1-877-311-8972, by sending an email to MotherToBaby@health.ucsd.edu, or go to www.mothertobaby.org/join-study.
- are breastfeeding or plan to breastfeed. It is not known if KESIMPTA passes into your breast milk. Talk to your healthcare provider about the best way to feed your baby if you take KESIMPTA.

Tell your healthcare provider about all the medicines you take, including prescription and over-the-counter medicines, vitamins, and herbal supplements.
Know the medicines you take. Keep a list of them to show your healthcare provider and pharmacist when you get a new medicine.

How should I use KESIMPTA?
See the detailed Instructions for Use that comes with KESIMPTA for information about how to prepare and inject a dose of KESIMPTA and how to properly throw away (dispose of) used KESIMPTA Sensoready pens or prefilled syringes.

- Use KESIMPTA exactly as your healthcare provider tells you to use it.
- KESIMPTA is given as an injection under your skin (subcutaneous injection), in your thigh or stomach-area (abdomen) by you or a caregiver. A caregiver may also give you an injection of KESIMPTA in your upper outer arm.
- Your healthcare provider will show you how to prepare and inject KESIMPTA the right way before you use it for the first time.
- Do not inject into areas where the skin is tender, bruised, red, scaly or hard. Avoid areas with moles, scars or stretch marks.
- The initial dosing is 20 mg of KESIMPTA given by subcutaneous injection at Weeks 0, 1, and 2. There is no injection at Week 3. Starting at Week 4 and then every month, the recommended dose is 20 mg of KESIMPTA administered by subcutaneous injection.
- If you miss an injection of KESIMPTA at Week 0, 1, or 2, talk to your healthcare provider. If you miss a monthly injection, give it as soon as possible without waiting until the next scheduled dose. After that, give your KESIMPTA injections a month apart.

What are the possible side effects of KESIMPTA?
KESIMPTA may cause serious side effects, including:
See “What is the most important information I should know about KESIMPTA?”

- Injection-related reactions. Injection-related reactions are a common side effect of KESIMPTA. Injecting KESIMPTA can cause injection-related reactions that can happen within 24 hours (1 day) following the first injection and with later injections. There are two kinds of reactions:
  - at or near the injection site: redness of the skin, swelling, itching and pain. Talk with your healthcare provider if you have any of these signs and symptoms.
  - that may happen when certain substances are released in your body: fever, headache, pain in the muscles, chills, tiredness, rash, hives, trouble breathing, swelling of the face, eyelids, lips, mouth, tongue and throat, and feeling faint, or chest tightness. Contact your healthcare provider right away if you experience any of these signs and symptoms, especially if they become worse or you have new severe signs of reactions after subsequent injections. It could be a sign of an allergic reaction, which can be serious.
- Low immunoglobulins. KESIMPTA may cause a decrease in some types of antibodies. Your healthcare provider will do blood tests to check your blood immunoglobulin levels.
- Liver damage. KESIMPTA may cause liver damage. Your healthcare provider will do blood tests to check your liver before you start KESIMPTA and while you take KESIMPTA if needed. Tell your healthcare provider right away if you have any symptoms of liver damage, such as:
  - yellowing of the skin and eyes (jaundice)
  - nausea
  - vomiting
  - unusual darkening of the urine
  - feeling tired or weak

The most common side effects of KESIMPTA include:

- upper respiratory tract infection, with symptoms, such as sore throat and runny nose, and headache. See “What is the most important information I should know about KESIMPTA?”
- headache

These are not all the possible side effects of KESIMPTA. Call your doctor for medical advice about side effects.
You may report side effects to FDA at 1-800-FDA-1088.

How should I store KESIMPTA?

- Store KESIMPTA in a refrigerator between 36°F to 46°F (2°C to 8°C).
- Keep KESIMPTA in the original carton until ready for use to protect from light.
- If needed, KESIMPTA may be stored for up to 7 days at room temperature, up to 86°F (30°C).
- Write the date taken out of the refrigerator in the space provided on the carton.
- If stored below 86°F (30°C), unused KESIMPTA may be returned to the refrigerator and must be used within the next 7 days. If this KESIMPTA is not used within those 7 days, then discard the medicine.
- Do not freeze KESIMPTA.
- Do not shake KESIMPTA.

Keep KESIMPTA and all medicines out of the reach of children.

General information about the safe and effective use of KESIMPTA.
Medicines are sometimes prescribed for purposes other than those listed in a Medication Guide. Do not use KESIMPTA for a condition for which it was not prescribed. Do not give KESIMPTA to other people, even if they have the same symptoms that you have. It may harm them. You can ask your pharmacist or healthcare provider for information about KESIMPTA that is written for health professionals.

What are the ingredients in KESIMPTA?
Active ingredient: ofatumumab
Inactive ingredients: Sensoready Pen and prefilled syringe: arginine, disodium edetate, polysorbate 80, sodium acetate trihydrate, sodium chloride, and Water for Injection. Hydrochloric acid may be added.
Distributed by: Novartis Pharmaceuticals Corporation, East Hanover, New Jersey 07936
For more information, go to www.novartis.us or call 1-888-669-6682.

This Medication Guide has been approved by the U.S. Food and Drug Administration.

Revised: 8/2025

T2025-50

INSTRUCTIONS FOR USE
KESIMPTA® [KEY-simp-ta]
(ofatumumab)
injection, for subcutaneous use
Sensoready® Pen

This Instructions for Use contains information on how to inject KESIMPTA Sensoready Pen.
Be sure that you read, understand, and follow this Instructions for Use before injecting KESIMPTA. Your healthcare provider should show you how to prepare and inject KESIMPTA the right way using the Sensoready Pen before you use it for the first time. Talk to your healthcare provider if you have any questions before you use KESIMPTA for the first time.
Important Information You Need to Know Before Injecting KESIMPTA Sensoready Pen.

- Do not use the KESIMPTA Sensoready Pen if either the seal on the outer carton or the seal on the KESIMPTA Sensoready Pen is broken. Keep the KESIMPTA Sensoready Pen in the sealed outer carton until you are ready to use it.
- Do not shake the KESIMPTA Sensoready Pen.
- If you drop your KESIMPTA Sensoready Pen, do not use it if it looks damaged, or if you dropped it with the cap removed.

Throw away (dispose of) the used KESIMPTA Sensoready Pen right away after use. Do not re-use a KESIMPTA Sensoready Pen. See “How should I dispose of used KESIMPTA Sensoready Pens?” at the end of this Instructions for Use.

How should I store KESIMPTA Sensoready Pen?

- Store your carton of KESIMPTA Sensoready Pen in a refrigerator, between 36°F to 46°F (2°C to 8°C).
- Keep KESIMPTA Sensoready Pen in the original carton until ready to use to protect from light.
- If needed, KESIMPTA Sensoready Pen may be stored for up to 7 days at room temperature, up to 86°F (30°C).
- Write the date taken out of the refrigerator in the space provided on the carton.
- If stored below 86°F (30°C), unused KESIMPTA may be returned to the refrigerator and must be used within the next 7 days. If this KESIMPTA is not used within those 7 days, then discard the medicine.
- Do not freeze KESIMPTA Sensoready Pen.

Keep KESIMPTA Sensoready Pen and all medicines out of the reach of children.
KESIMPTA Sensoready Pen parts (see Figure A):
Figure A
The KESIMPTA Sensoready Pen is shown with the cap removed. Do not remove the cap until you are ready to inject.

What you need for your injection:
Included in the carton:
A new KESIMPTA Sensoready Pen (see Figure B).

Figure B

Not included in the carton (see Figure C):

- 1 alcohol wipe
- 1 cotton ball or gauze
- Sharps disposal container

See “How should I dispose of used KESIMPTA Sensoready Pens?” at the end of this Instructions for Use.

Figure C

Before your injection
Take the KESIMPTA Sensoready Pen out of the refrigerator 15 to 30 minutes before injecting to allow it to reach room temperature.
Step 1. Important safety checks before you inject (see Figure D):

- Look through the viewing window. The liquid should be clear to slightly cloudy.

Do not use if the liquid contains visible particles or is cloudy.
You may see a small air bubble, which is normal.

- Look at the expiration date (EXP) on your KESIMPTA Sensoready Pen. Do not use your pen if the expiration date has passed.

Contact your pharmacist or healthcare provider if your pen fails any of these checks.

Figure D

Step 2. Choose your injection site:

- The recommended site is the front of the thighs. You may also use the lower stomach area (lower abdomen), but not the area 2 inches around the navel (belly button) (see Figure E).
- Do not inject into areas where the skin is tender, bruised, red, scaly, or hard. Avoid areas with moles, scars or stretch marks.
- If a caregiver or healthcare provider is giving you your injection, they may also inject into your outer upper arm (see Figure F).

Figure E
Figure F (Caregiver and healthcare provider only)

Step 3. Clean your injection site:

- Wash your hands with soap and water.
- Using a circular motion, clean the injection site with the alcohol wipe. Leave it to dry before injecting (see Figure G).
- Do not touch the cleaned area again before injecting.

Figure G

Your injection
Step 4. Remove the cap:

- Only remove the cap when you are ready to use the KESIMPTA Sensoready Pen.
- Twist off the cap in the direction of the arrow (see Figure H).
- Throw away the cap. Do not try to re-attach the cap.
- Use the KESIMPTA Sensoready Pen within 5 minutes of removing the cap.

You may see a few drops of medicine come out of the needle. This is normal.

Figure H

Step 5. Hold your KESIMPTA Sensoready Pen:

- Hold the KESIMPTA Sensoready Pen at 90 degrees to the cleaned injection site (see Figure I).

Figure I

Important: During the injection you will hear 2 loud clicks:

- The 1st click indicates that the injection has started
- A 2nd click will indicate that the injection is almost complete

You must keep holding the KESIMPTA Sensoready Pen firmly against the skin until the green indicator fills the window and stops moving.

Step 6. Start your injection:

- Press the KESIMPTA Sensoready Pen firmly against the skin to start the injection (see Figure J).
- The 1st click indicates the injection has started.
- Keep holding the KESIMPTA Sensoready Pen firmly against your skin.
- The green indicator shows the progress of the injection.

Figure J

Step 7. Complete your injection:

- Listen for the 2nd click. This indicates that the injection is almost complete.
- Check to see if the green indicator fills the window and has stopped moving (see Figure K).
- The KESIMPTA Sensoready Pen can now be removed (see Figure L).

Figure K

After your injection

- In case the green indicator does not fill the window, it means the medicine has not been delivered. Contact your healthcare provider if the green indicator is not visible.
- There may be a small amount of blood at the injection site. You can press a cotton ball or gauze over the injection site and hold it for 10 seconds. Do not rub the injection site. You may cover the injection site with a small adhesive bandage, if needed.

Figure L

How should I dispose of used KESIMPTA Sensoready® Pens?
Step 8. Put your used KESIMPTA Sensoready Pen in an FDA-cleared sharps disposal container right away after use (see Figure M). Do not throw away (dispose of) your used KESIMPTA Sensoready Pen in your household trash.
If you do not have an FDA-cleared sharps disposal container, you may use a household container that is:

- made of a heavy-duty plastic,
- can be closed with a tight-fitting, puncture-resistant lid, without sharps being able to come out,
- upright and stable during use,
- leak-resistant, and
- properly labeled to warn of hazardous waste inside the container.

When your sharps disposal container is almost full, you will need to follow your community guidelines for the right way to dispose of your sharps disposal container. There may be state or local laws about how you should throw away used needles, syringes and pens. For more information about safe sharps disposal, and for specific information about sharps disposal in the state that you live in, go to the FDA’s website at: http://www.fda.gov/safesharpsdisposal.
Keep the sharps container out of the reach of children.
Manufactured by:
Novartis Pharmaceuticals Corporation
East Hanover, NJ 07936
U.S. License No.: 1244

Figure M

This Instructions for Use has been approved by the U.S. Food and Drug Administration.

Revised: 9/2022

T2022-54

INSTRUCTIONS FOR USE
KESIMPTA® [KEY-simp-ta]
(ofatumumab)
injection, for subcutaneous use
Prefilled Syringe

This Instructions for Use contains information on how to inject KESIMPTA Prefilled Syringe.
Be sure that you read, understand, and follow this Instructions for Use before injecting KESIMPTA prefilled syringe. Your healthcare provider should show you how to prepare and inject KESIMPTA the right way before using the prefilled syringe the first time. Talk to your healthcare provider if you have any questions.
Important Information You Need to Know Before Injecting KESIMPTA prefilled syringe.

- Do not use the KESIMPTA prefilled syringe if either the seal on the outer carton or the seal of the blister is broken. Keep the KESIMPTA prefilled syringe in the sealed carton until you are ready to use it.
- Do not shake the KESIMPTA prefilled syringe.
- The KESIMPTA prefilled syringe has a needle guard that will be activated to cover the needle after the injection is finished. The needle guard will help to prevent needle stick injuries to anyone who handles the KESIMPTA prefilled syringe after injection.
- Do not remove the needle cap until just before you give the injection.
- Avoid touching the syringe guard wings before use. Touching them may cause the needle guard to be activated too early.
- Do not use if the prefilled syringe has been dropped onto a hard surface or dropped after removing the needle cap.
- Throw away (dispose of) the used KESIMPTA prefilled syringe right away after use. Do not re-use a KESIMPTA prefilled syringe. See "How should I dispose of used KESIMPTA prefilled syringes?” at the end of these Instructions for Use.

How should I store KESIMPTA Prefilled Syringe?

- Store your carton of the KESIMPTA prefilled syringe in a refrigerator, between 36°F to 46°F (2°C to 8°C).
- Keep the KESIMPTA prefilled syringe in the original carton until ready to use to protect from light.
- If needed, KESIMPTA prefilled syringe may be stored for up to 7 days at room temperature, up to 86°F (30°C).
- Write the date taken out of the refrigerator in the space provided on the carton.
- If stored below 86°F (30°C), unused KESIMPTA may be returned to the refrigerator and must be used within the next 7 days. If this KESIMPTA is not used within those 7 days, then discard the medicine.
- Do not freeze the KESIMPTA prefilled syringe.

Keep KESIMPTA Prefilled Syringe and all medicines out of the reach of children.

KESIMPTA prefilled syringe parts (see Figure A):
Figure A

What you need for your injection
Included in the carton:
A new KESIMPTA prefilled syringe.
Not included in the carton (see Figure B):

- 1 alcohol wipe
- 1 cotton ball or gauze
- Sharps disposal container

See “How should I dispose of used KESIMPTA prefilled syringe?” at the end of these Instructions for Use.

Figure B

Prepare the KESIMPTA prefilled syringe
Step 1. Find a clean, well-lit, flat work surface.
Step 2. Take the carton containing the KESIMPTA prefilled syringe out of the refrigerator and leave it unopened on your work surface for about 15 to 30 minutes so that it reaches room temperature.
Step 3. Wash your hands well with soap and water.
Step 4. Remove the KESIMPTA prefilled syringe from the outer carton and take it out of the blister by holding the syringe guard body.
Step 5. Look through the viewing window on the KESIMPTA prefilled syringe. The liquid inside should be clear to slightly cloudy. You may see a small air bubble in the liquid, which is normal. Do not use the KESIMPTA prefilled syringe if the liquid contains particles or is cloudy.
Step 6. Do not use the KESIMPTA prefilled syringe if it is broken. Return the KESIMPTA prefilled syringe and the package it came in to the pharmacy.
Step 7. Do not use the KESIMPTA prefilled syringe if the expiration date has passed (see Figure C). Return the expired KESIMPTA prefilled syringe and the package it came in to the pharmacy.

Figure C

Choose and clean the injection site

- Areas of your body that you may use as injection sites include:
  - the front of your thighs (see Figure D)
  - the lower stomach-area (abdomen), but not the area 2 inches around your navel (belly button) (see Figure D)
  - your outer upper arms, if a healthcare provider or caregiver is giving you the injection (see Figure E)
- Do not inject into areas where the skin is tender, bruised, red, scaly, or hard. Avoid areas with moles, scars, or stretch marks.

Step 8. Using a circular motion, clean the injection site with the alcohol wipe. Leave it to dry before injecting. Do not touch the cleaned area again before injecting.

Figure D
Figure E (Caregiver and healthcare provider only)

Giving your injection
Step 9. Carefully remove the needle cap from the KESIMPTA prefilled syringe (see Figure F). Throw away the needle cap. You may see a drop of liquid at the end of the needle. This is normal.

Figure F

Step 10. With one hand, gently pinch the skin at the injection site. With your other hand insert the needle into your skin at an angle of about 45 degrees as shown (see Figure G). Push the needle all the way in to make sure that you inject your full dose.

Figure G

Step 11. Hold the KESIMPTA prefilled syringe finger grips as shown (see Figure H). Slowly press down on the plunger head as far as it will go, so that the plunger head is completely between the syringe guard wings.
Continue to press fully on the plunger head for an additional 5 seconds. Hold the syringe in place for the full 5 seconds.

Figure H

Step 12. Slowly release the plunger head until the needle is covered (see Figure I), and then remove the syringe from the injection site.
Step 13. There may be a small amount of blood at the injection site. You can press a cotton ball or gauze over the injection site and hold it for 10 seconds. Do not rub the injection site. You may cover the injection site with a small adhesive bandage, if needed.

Figure I

How should I dispose of used KESIMPTA prefilled syringes?
Step 14. Put your used KESIMPTA prefilled syringe in an FDA-cleared sharps disposal container right away after use (see Figure J). Do not throw away (dispose of) your used KESIMPTA prefilled syringe in your household trash. Never try to reuse your KESIMPTA prefilled syringe.
If you do not have an FDA-cleared sharps disposal container, you may use a household container that is:

- made of a heavy-duty plastic,
- can be closed with a tight-fitting, puncture-resistant lid, without sharps being able to come out,
- upright and stable during use,
- leak-resistant, and
- properly labeled to warn of hazardous waste inside the container.

When your sharps disposal container is almost full, you will need to follow your community guidelines for the right way to dispose of your sharps disposal container. There may be state or local laws about how you should throw away used needles, syringes, and prefilled syringes. For more information about safe sharps disposal, and for specific information about sharps disposal in the state that you live in, go to the FDA’s website at: http://www.fda.gov/safesharpsdisposal.
Keep the sharps container out of the reach of children.
Manufactured by:
Novartis Pharmaceuticals Corporation
East Hanover, NJ 07936
U.S. License No.: 1244

Figure J

This Instructions for Use has been approved by the U.S. Food and Drug Administration.

Revised: 4/2024

T2024-33

PRINCIPAL DISPLAY PANEL

NDC 0078-1007-68

Rx only

Kesimpta®
(ofatumumab)
Injection

20 mg/0.4 mL

Single-dose Prefilled Sensoready® Pen
For Subcutaneous Use Only

Sterile Solution - Contains No Preservatives

Carton contains: 1 Single-dose Prefilled Sensoready® Pen,
Prescribing Information, Instructions for Use, and Medication Guide

Attention: Dispense with enclosed Medication Guide.

REFRIGERATE

NOVARTIS